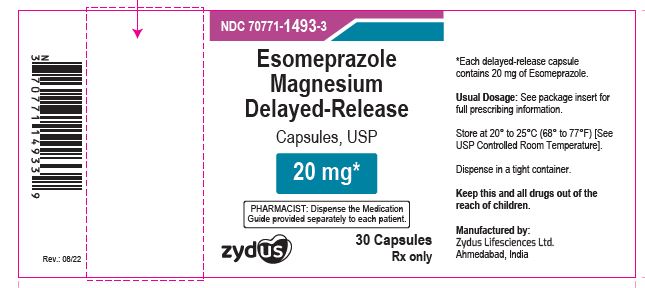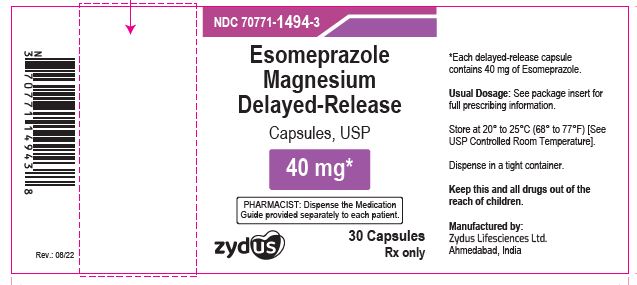 DRUG LABEL: esomeprazole magnesium
NDC: 70771-1493 | Form: CAPSULE, DELAYED RELEASE
Manufacturer: Zydus Lifesciences Limited
Category: prescription | Type: HUMAN PRESCRIPTION DRUG LABEL
Date: 20241128

ACTIVE INGREDIENTS: ESOMEPRAZOLE MAGNESIUM DIHYDRATE 20 mg/1 1
INACTIVE INGREDIENTS: ALCOHOL; AMMONIA; BUTYL ALCOHOL; FD&C BLUE NO. 1; FD&C RED NO. 3; FERROSOFERRIC OXIDE; GELATIN; GLYCERYL MONO- AND DICAPRYLOCAPRATE; HYDROXYPROPYL CELLULOSE (90000 WAMW); ISOPROPYL ALCOHOL; MAGNESIUM OXIDE; MAGNESIUM STEARATE; MANNITOL; METHACRYLIC ACID; POLYSORBATE 80; POTASSIUM HYDROXIDE; POVIDONE K30; PROPYLENE GLYCOL; SHELLAC; SODIUM LAURYL SULFATE; STARCH, CORN; SUCROSE; TALC; TITANIUM DIOXIDE; TRIETHYL CITRATE; WATER

ESOMEPRAZOLE MAGNESIUM DELAYED-RELEASE CAPSULES

PACKAGE LABEL.PRINCIPAL DISPLAY PANEL

NDC 70771-1493-3

Esomeprazole Magnesium Delayed-release Capsules, USP

20 mg

30 Capsules

NDC 70771-1494-3

Esomeprazole Magnesium Delayed-release Capsules, USP

40 mg

30 Capsules